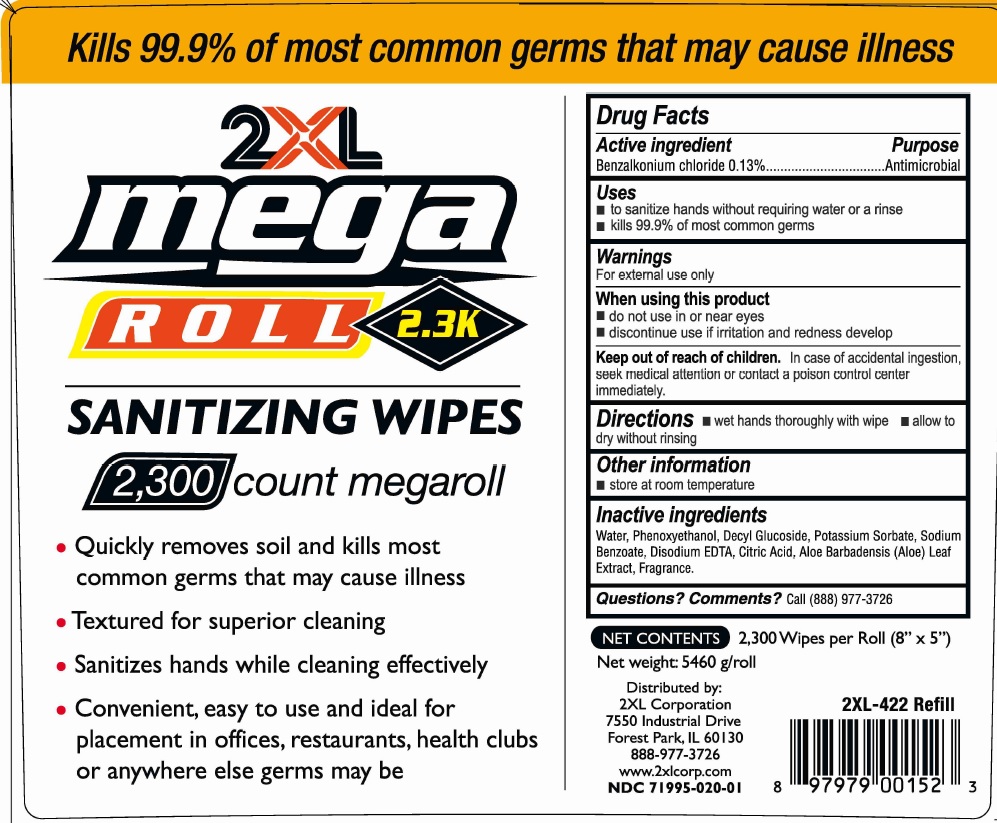 DRUG LABEL: 2xl Mega Roll sanitizing wipes 2300 count megaroll
NDC: 71995-002 | Form: CLOTH
Manufacturer: 2XL Corporation
Category: otc | Type: HUMAN OTC DRUG LABEL
Date: 20221129

ACTIVE INGREDIENTS: BENZALKONIUM CHLORIDE 1.3 mg/1 mL
INACTIVE INGREDIENTS: WATER; PHENOXYETHANOL; DECYL GLUCOSIDE; POTASSIUM SORBATE; SODIUM BENZOATE; EDETATE DISODIUM ANHYDROUS; CITRIC ACID MONOHYDRATE; ALOE VERA LEAF

2xl Mega Roll sanitizing wipes 2300 count megaroll

Active ingredient

Benzalkonium Chloride 0.13%

Purpose

Antimicrobial

Uses

- to sanitize hands without requiring water or a rinse
- kills 99.9% of most common germs

Warnings

For external use only

When using this product

- do not use in or near eyes
- discontinue use if irritation and redness develop

Keep out of reach of children.

In case of accidental ingestion, seek medical attention or contact a poison control center immediately.

Directions

- wet hands thoroughly with wipe
- allow to dry without rinsing

Other information

- store at room temperature

Inactive ingredients

Water, Phenoxyethanol, Decyl Glucoside, Potassium Sorbate, Sodium Benzoate, Disodium EDTA, Citric Acid, Aloe Barbadensis (Aloe) Leaf Extract, Fragrance.

Questions? Comments?

Call (888) 977-3726